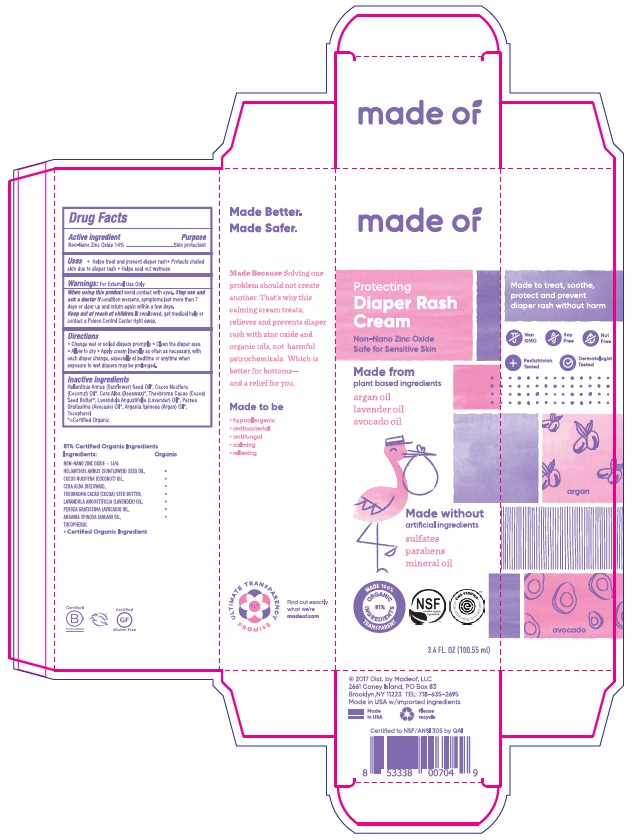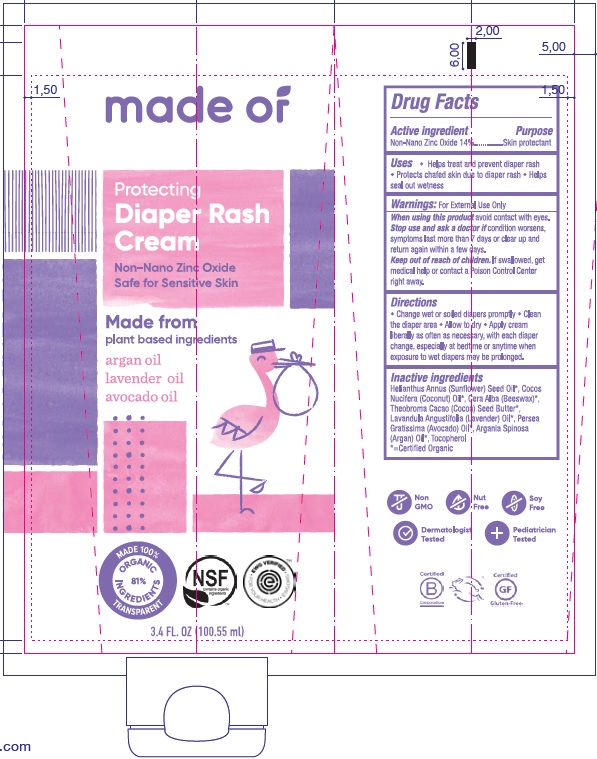 DRUG LABEL: Diaper Cream
NDC: 62932-181 | Form: OINTMENT
Manufacturer: Private Label Select Ltd CO
Category: otc | Type: HUMAN OTC DRUG LABEL
Date: 20181123

ACTIVE INGREDIENTS: ZINC OXIDE 14 g/100 g
INACTIVE INGREDIENTS: HELIANTHUS ANNUUS SEED WAX; COCONUT OIL; LAVENDER OIL; AVOCADO OIL; YELLOW WAX; THEOBROMA GRANDIFLORUM SEED BUTTER; TOCOPHEROL; ARGAN OIL

made of Diaper Rash Cream